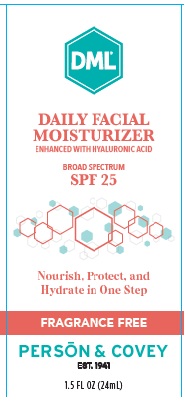 DRUG LABEL: Daily Facial Moisturizer
NDC: 0096-0721 | Form: CREAM
Manufacturer: Person and Covey
Category: otc | Type: HUMAN OTC DRUG LABEL
Date: 20260122

ACTIVE INGREDIENTS: HOMOSALATE 0.06 g/1 g; AVOBENZONE 0.03 g/1 g; OCTINOXATE 0.075 g/1 g; OCTOCRYLENE 0.015 g/1 g
INACTIVE INGREDIENTS: VINYLPYRROLIDONE/EICOSENE COPOLYMER; WATER; PETROLATUM; CETYL PHOSPHATE; CYCLOPENTASILOXANE; ALLANTOIN; CARBOMER 940; DIMETHICONE 1000; SILICON DIOXIDE; GLYCERYL STEARATE/PEG-100 STEARATE; SODIUM HYDROXIDE; STEARIC ACID; PROPYLENE GLYCOL DIETHYLHEXANOATE; SODIUM HYALURONATE; MAGNESIUM ALUMINUM SILICATE TYPE IA; DIMETHICONE 200; CITRIC ACID MONOHYDRATE; GLYCERIN; BENZYL ALCOHOL

DML Daily Facial Moisturizer

Uses

-Moisturizes and helps to relieve irritated and sensitive skin

-Higher SPF gives more sunburn protection

-Water resistant

Keep Out of the Reach of Children

If swallowed, get medical help or contact a Poison Control Center right away.

Warnings

For external use only

.Stop Use

Stop Use and ask a Doctor if a rash rash or irritation develops and lasts

Questions

Questions? Please call 1 (800) 423-2341

Inactive Ingredients

Purified Water, Propylene Glycol Dioctanoate, Petrolatum, Glycerin, Glyceryl Stearate, PEG-100 Stearate, DEA-Cetyl Phosphate, Stearic Acid, Hyaluronic Acid, Benzyl Alcohol, Dimethicone, Cyclomethicone, PVP/Eicosene Copolymer, Silica, Sodium Carbomer 941, Allantoin, Disodium EDTA, Magnesium Aluminum Silicate

Other Information

-High sun protection product

-Sun Alert: limiting sun exposure, wearing sun protective clothing and using sunscreens may reduce the risk of skin aging, skin cancer and other harmful effects of the sun.

-Avoid exposure to extreme heat or cold.

Active Ingredients

Octinoxate......7.5% Sunscreen

Homosalate....6.0% Sunscreen

Avobenzone...3.0% Sunscreen

Octocrylene....1.5% Sunscreen

Directions

-Apply DML Daily Facial Moisturizer liberally and evenly 15-20 minutes before sun exposure and message in gently, allowing it to dry. Reapply as needed or as directed by your Dermatologist.

-DML Daily Facial is an excellant make-up base.

Purpose

Sunscreen